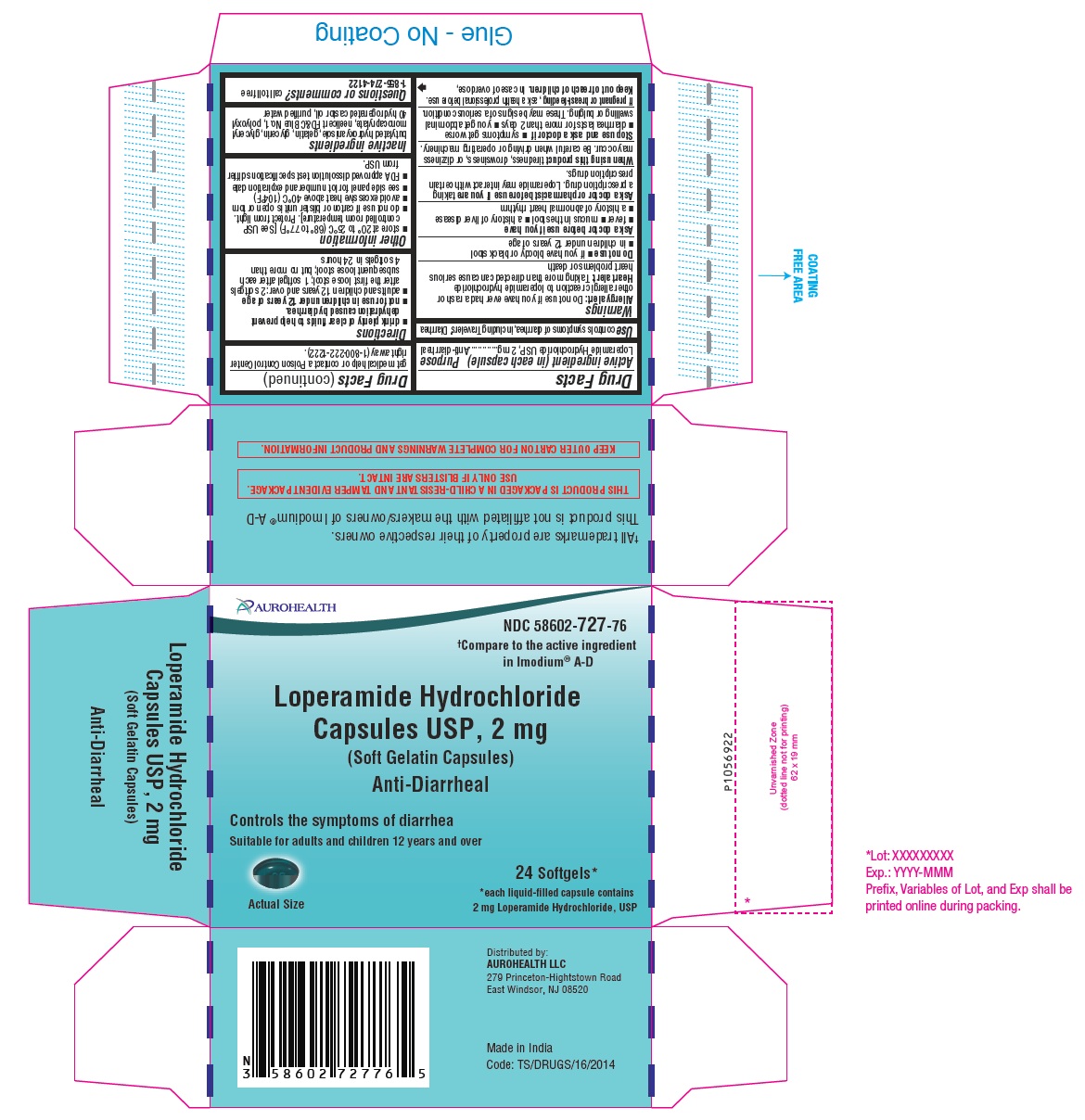 DRUG LABEL: LOPERAMIDE HYDROCHLORIDE
NDC: 58602-727 | Form: CAPSULE, LIQUID FILLED
Manufacturer: Aurohealth LLC
Category: otc | Type: Human OTC Drug Label
Date: 20260105

ACTIVE INGREDIENTS: LOPERAMIDE HYDROCHLORIDE 2 mg/1 1
INACTIVE INGREDIENTS: BUTYLATED HYDROXYANISOLE; GELATIN TYPE B BOVINE (160 BLOOM); GLYCERIN; GLYCERYL MONOCAPRYLATE; FD&C BLUE NO. 1; POLYOXYL 40 HYDROGENATED CASTOR OIL; WATER

Drug Facts

Active ingredient (in each capsule)

Loperamide Hydrochloride USP, 2 mg

Purpose

Anti-diarrheal

Use

controls symptoms of diarrhea, including Travelers' Diarrhea

Warnings

Allergy alert: Do not use if you have ever had a rash or other allergic reaction to loperamide hydrochloride

Heart alert: Taking more than directed can cause serious heart problems or death

Do not use

- if you have bloody or black stool
- in children under 12 years of age

Ask a doctor before use if you have

- fever
- mucus in the stool
- a history of liver disease
- a history of abnormal heart rhythm

Ask a doctor or pharmacist before use if you are taking a prescription drug. Loperamide may interact with certain prescription drugs.

When using this product

tiredness, drowsiness, or dizziness may occur. Be careful when driving or operating machinery.

Stop use and ask a doctor if

- symptoms get worse
- diarrhea lasts for more than 2 days
- you get abdominal swelling or bulging. These may be signs of a serious condition.

PREGNANCY OR BREAST FEEDING

If pregnant or breast-feeding, ask a health professional before use.

Keep out of reach of children. In case of overdose, get medical help or contact a Poison Control Center right away (1-800-222-1222).

Directions

- drink plenty of clear fluids to help prevent dehydration caused by diarrhea.
- not for use in children under 12 years of age
- adults and children 12 years and over: 2 softgels after the first loose stool; 1 softgel after each subsequent loose stool; but no more than 4 softgels in 24 hours

Other information

- store at 20° to 25°C (68° to 77°F) [See USP controlled room temperature]. Protect from light.
- do not use if carton or blister unit is open or torn
- avoid excessive heat above 40°C (104°F)
- see side panel for lot number and expiration date
- FDA approved dissolution test specifications differ from USP.

Inactive ingredients

butylated hydroxyanisole, gelatin, glycerin, glyceryl monocaprylate, neelicert FD&C Blue No.1, polyoxyl 40 hydrogenated castor oil, purified water

Questions or comments?

call toll free 1-855-274-4122

Distributed by:
AUROHEALTH LLC
279 Princeton-Hightstown Road
East Windsor, NJ 08520

Made in India

Code: TS/DRUGS/16/2014

PACKAGE LABEL-PRINCIPAL DISPLAY PANEL - 2 mg (24 Softgels) Blister Carton Label

AUROHEALTH
NDC 58602-727-76
†Compare to the active ingredient
in Imodium® A-D
Loperamide Hydrochloride
Capsules USP, 2 mg
(Soft Gelatin Capsules)
Anti-Diarrheal

Controls the symptoms of diarrhea
Suitable for adults and children 12 years and over
Actual Size
24 Softgels*
*each liquid-filled capsule contains
2 mg Loperamide Hydrochloride, USP